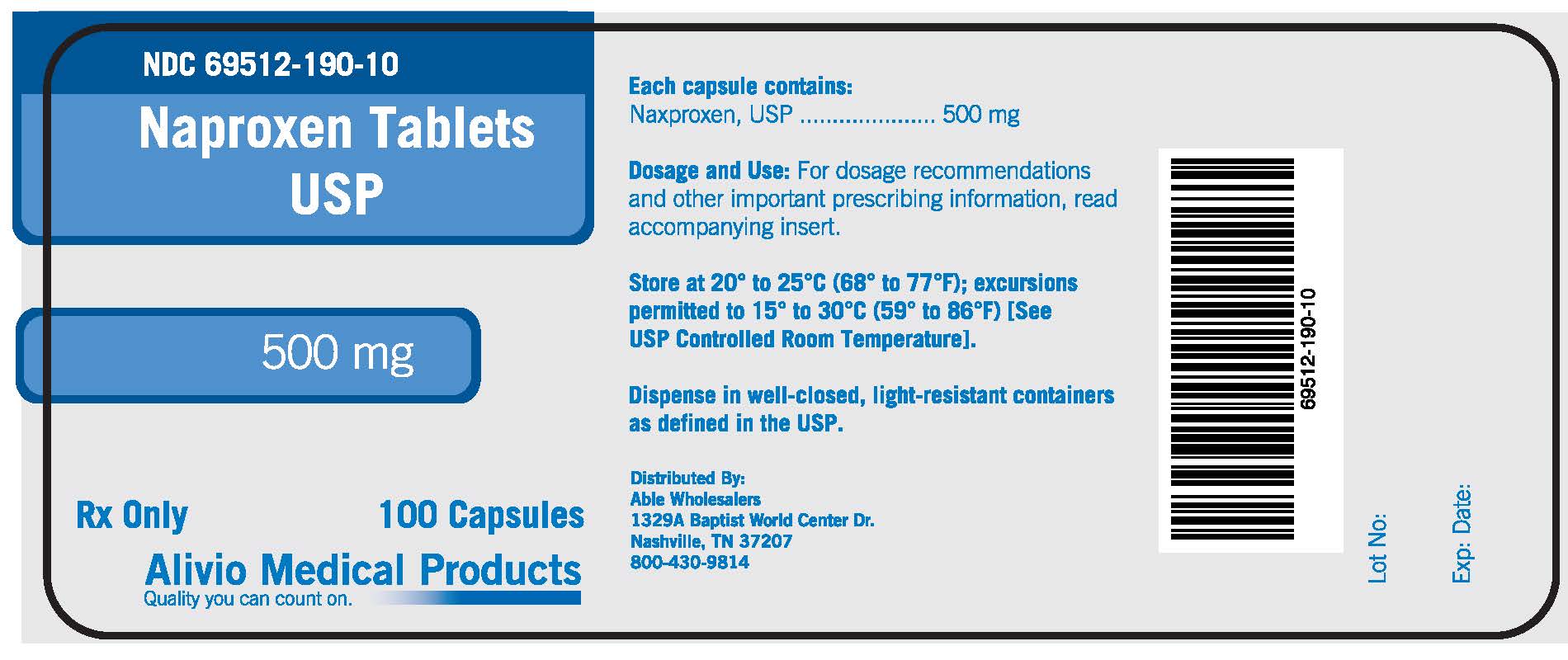 DRUG LABEL: Naproxen
NDC: 69512-190 | Form: TABLET
Manufacturer: Alivio Medical Products, LLC
Category: prescription | Type: HUMAN PRESCRIPTION DRUG LABEL
Date: 20151015

ACTIVE INGREDIENTS: NAPROXEN 500 mg/500 mg
INACTIVE INGREDIENTS: CROSCARMELLOSE SODIUM; POVIDONES; MAGNESIUM STEARATE

Drug Facts

DESCRIPTION

Each capsule contains:

Naxproxen, ESP ..........500 mg

DESCRIPTION

Dosage and Use: For dosage recommendations

and other important prescribing information, read accompanying insert.

STORAGE AND HANDLING

Store at 20 to 25 C (68 to 77 F); excursions

permitted to 15 to 30 C (59 to 86 F)[See

USP Controlled Room Temperature]

Dispense in well-closed, light-resistant containers

as defined in the USP.

BOXED WARNING

Cardiovascular Risk

-NSAIDs may cause an increased risk of serious cardiovascular thrombotic events,

myocardial infarction, and stroke, which can be fatal.

-Naproxen as Naproxen Tablets, USP is contraindicated for the treatment of peri-operative

pain in the setting of coronary artery bypass graft (CABG) surgery (see WARNINGS).

Gastrointestinal Risk

-NSAIDs may cause an increased risk of serious gastrointestinal adverse events including

bleeding, ulceration. and perforation of the stomach or intestines, which can be fatal.

DESCRIPTION

Naproxen, USP is a proprionic acid derivative related to the arylacetic acid group of nonsteroidal anti-inflammatory drugs.

CLINICAL PHARMACOLOGY

Pharmacodynamics - Naproxen is a nonsteroidal anti-inflammatory drug (NSAID) with analgesic and

antipyretic properties.

CLINICAL STUDIES

General Information - Naproxen has been studied in patients with rheumatoid arthritis, osteoarthritis,

juvenile arthritis, ankylosing spondylitis, tendonitis and bursitis, and acute gout.

INDICATIONS AND USAGE

Carefully consider the potential benefits and risks of naproxen tablets, USP and other treatments

before deciding to sue naproxen tablets, USP.

CONTRAINDICATIONS

Naproxen tablets, USP are contraindicated in patients with known hypersensitivity to naproxen, USP.

WARNINGS

Cardiovascular Effects - Cardiovascular Thrombotic Events Clinical trials of several COX-2 selective

and non-selective NSAIDs of up to three years duration have shown an increased risk of serious cardiovascular (CV)

thrombotic events, myocardial infarction, and stroke, which can be fatal.

PRECAUTIONS

General - Naproxen - containing products such as naproxen tablets, and other naproxen products should

not be used concomitantly since they all circulate in the plasma as the naproxin anion.

ADVERSE REACTIONS

Adverse reactions reported in controlled clinical trials in 960 patients treated for rheumatoid arthritis

or osteoarthritis are listed below.

OVERDOSAGE

Symptoms and Signs Significant naproxen overdosage may be characterized by lethargy, dizziness,

drowsiness, epigastric pain, abdominal discomfort, heartburn, indigestion, nausea, transient alterations in liver function,

hypoprothrombinemia, renal dysfunction, metabolic acidosis, apnea, disorientation or vomiting.

DOSAGE AND ADMINISTRATION

Carefully consider the potential benefits and risks of naproxen tablets, USP and other treatment

options before deciding to use naproxen tablets, USP.

PATIENT INFORMATION

MEDICATION GUIDE FOR NONSTEROIDAL ANTI-INFLAMMATORY DRUGS (NSAIDS)

(See the end of this Medication Guide for a list of prescription NSAID medicines.)